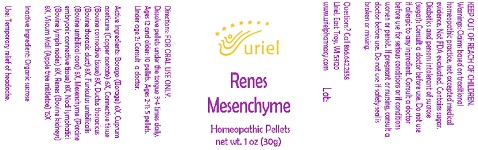 DRUG LABEL: Renes Mesenchyme
NDC: 48951-8381 | Form: PELLET
Manufacturer: Uriel Pharmacy Inc.
Category: homeopathic | Type: HUMAN OTC DRUG LABEL
Date: 20210730

ACTIVE INGREDIENTS: CUPRIC ACETATE 6 [hp_X]/1 1; BOS TAURUS CONJUNCTIVA 8 [hp_X]/1 1; BOS TAURUS CARTILAGE 8 [hp_X]/1 1; BORAGE 6 [hp_X]/1 1; BOS TAURUS LYMPH VESSEL 8 [hp_X]/1 1; SUS SCROFA UMBILICAL CORD 8 [hp_X]/1 1; PORK KIDNEY 8 [hp_X]/1 1; VISCUM ALBUM FRUITING TOP 15 [hp_X]/1 1
INACTIVE INGREDIENTS: SUCROSE

Renes Mesenchyme

INDICATIONS AND USAGE

Directions: FOR ORAL USE ONLY.

DOSAGE AND ADMINISTRATION

Dissolve pellets under the tongue 3-4 times daily. Ages 12 and older: 10 pellets. Ages 2-11: 5 pellets. Under age 2: Consult a doctor.

ACTIVE INGREDIENT

Active Ingredients: Borago (Borage) 6X, Cuprum aceticum (Copper acetate) 6X, Connective tissue (Bovine connective tissue) 8X, Ductus thoracicus (Bovine thoracic duct) 8X,Funiculus umbilicalis (Bovine umbilical cord) 8X, Mesenchyme (Porcine embryonic connective tissue) 8X, Nodi lymphatici (Bovine lymph nodes) 8X, Renes (Bovine kidneys) 8X, Viscum Mali (Apple tree mistletoe) 15X

Inactive Ingredient: Organic sucrose

PURPOSE

Use: Temporary relief of headache.

KEEP OUT OF REACH OF CHILDREN.

WARNINGS

Warnings: Claims based on traditional homeopathic practice, not accepted medical evidence. Not FDA evaluated. Contains sugar.
Diabetics and persons intolerant of sucrose (sugar): Consult a doctor before use. Do not use if allergic to any ingredient. Consult a doctor before use for serious conditions or if conditions worsen or persist. If pregnant or nursing, consult a doctor before use.
Do not use if safety seal is broken or missing.

Questions? Call 866.642.2858
Uriel, East Troy, WI 53120
www.urielpharmacy.com Lot: